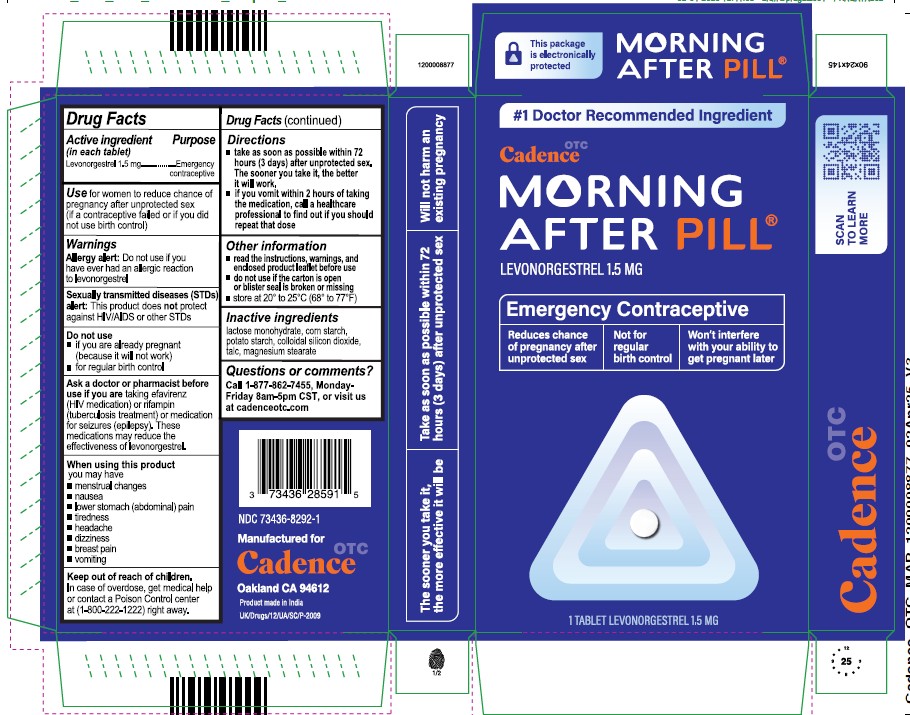 DRUG LABEL: Morning After Pill
NDC: 73436-8292 | Form: TABLET
Manufacturer: Cadence Health Inc
Category: otc | Type: HUMAN OTC DRUG LABEL
Date: 20250415

ACTIVE INGREDIENTS: LEVONORGESTREL 1.5 mg/1 1
INACTIVE INGREDIENTS: STARCH, CORN; MAGNESIUM STEARATE; SILICON DIOXIDE; TALC; STARCH, POTATO; LACTOSE MONOHYDRATE

Active Ingredient (in each tablet)

Levonorgestrel 1.5 mg

Purpose

Emergency contraceptive

Use

for women to reduce chance of pregnancy after unprotected sex (if a contraceptive failed or if you did not use birth control)

Warnings

Allergy Alert: Do not use if you have ever had an allergic reaction to levonorgestrel

Sexually transmitted diseases (STDs) Alert: This product does not protect against HIV/AIDS or other STDs

Do not use

- if you are already pregnant (because it will not work)
- for regular birth control

Ask a doctor or pharmacist before use if you are taking efavirenz (HIV medication) or rifampin (tuberculosis treatment) or medication for seizures (epilepsy). These medications may reduce the effectiveness of levonorgestrel.

When using this product you may have

- menstrual changes
- nausea
- lower stomach (abdominal) pain
- tiredness
- headaches
- dizziness
- breast pain
- vomiting

Keep out of reach of children.

In case of overdose, get medical help or contact a Poison Control center at (1-800-222-1222) right away.

Directions

- take as soon as possible within 72 hours (3 days) after unprotected sex. The sooner you take it, the better it will work.
- if you vomit within 2 hours of taking the medication, call a healthcare professional to find out if you should repeat that dose

Other information

- read the instructions, warnings, and enclosed product leaflet before use
- do not use if the carton is open or blister seal is broken or missing
- store at 20° to 25°C (68° to 77°F)

Inactive ingredients

lactose monohydrate, corn starch potato starch, colloidal silicon dioxide, talc, magnesium stearate

Questions or comments?

Call 1-877-862-7455, Monday - Friday 8am - 5pm CST, or visit us at cadenceotc.com

NDC 73436-8292-1

Manufactured for:
Cadence OTC

Oakland CA 94612

Product made in India

UK/Drugs/12/UA/SC/P-2009

PACKAGE LABEL

1. NDC 73436-8292-1

Morning After Pill

Levonorgestrel 1.5 mg

Emergency contraceptive

Reduces chance of pregnancy after unprotected sex

Not for regular birth control

Won't interefere with your ability to get pregnant later

- The sooner you take it, the more effective it will be
- Take as soon as possible within 72 hours (3 days) after unprotected sex
- Will not harm an existing pregnancy

1 TABLET LEVONORGESTREL 1.5MG